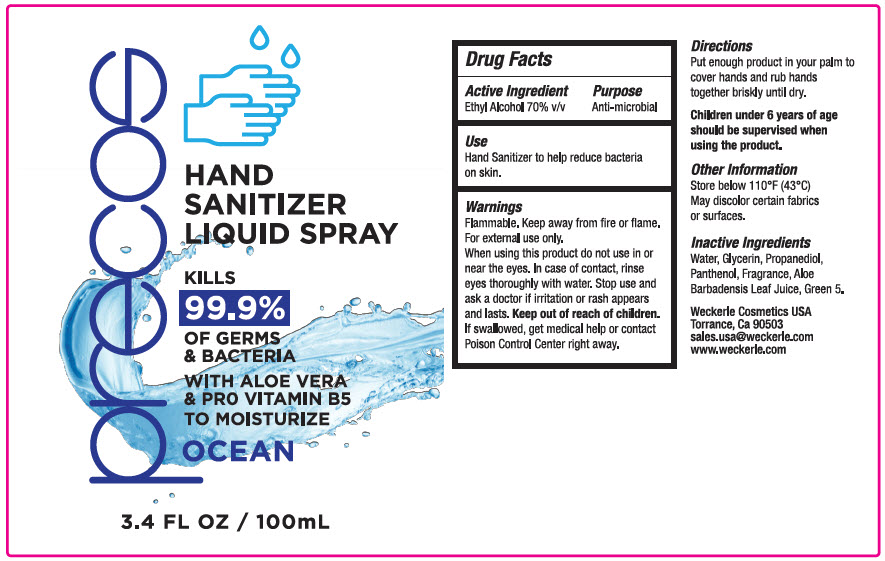 DRUG LABEL: HAND SANITIZER liquid
NDC: 62516-002 | Form: AEROSOL, SPRAY
Manufacturer: Weckerle Cosmetics LLC
Category: otc | Type: HUMAN OTC DRUG LABEL
Date: 20200713

ACTIVE INGREDIENTS: Alcohol 70 mL/100 mL
INACTIVE INGREDIENTS: Water; Glycerin; Propanediol; Panthenol; Aloe Vera Leaf; D&C Green No. 5

HAND SANITIZER LIQUID SPRAY

Drug Facts

Active Ingredient

Ethyl Alcohol 70% v/v

Purpose

Anti-microbial

Use

- Hand Sanitizer to help reduce bacteria on skin

Warnings

Flammable. Keep away from fire or flame.

For external use only

When using this product do not use in or near the eyes. In case of contact, rinse eyes thoroughly with water.

Stop use and ask a doctor if irritation or rash appears and lasts.

Keep out of reach of children. If swallowed, get medical help or contact Poison Control Center right away.

Directions

- Put enough product in your palm to cover hands and rub hands together briskly until dry.
- Children under 6 years of age should be supervised when using the product.

Other Information

- Store below 110°F (43°C)
- May discolor certain fabrics or surfaces

Inactive Ingredients

Water , Glycerin, Propanediol, Panthenol, Fragrance, Aloe Barbadensis Leaf Juice, Green 5.

PRINCIPAL DISPLAY PANEL - 100 mL Bottle Label

precos

HAND
SANITIZER
LIQUID SPRAY

KILLS
99.9%
OF GERMS
& BACTERIA

WITH ALOE VERA
& PRO VITAMIN B5
TO MOISTURIZE

OCEAN

3.4 FL OZ / 100mL